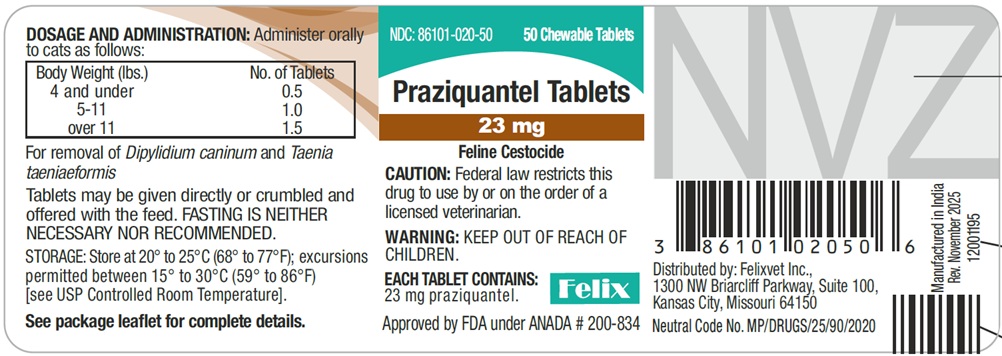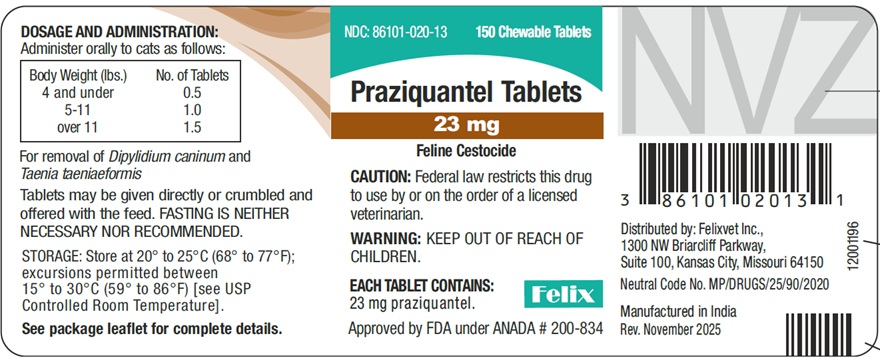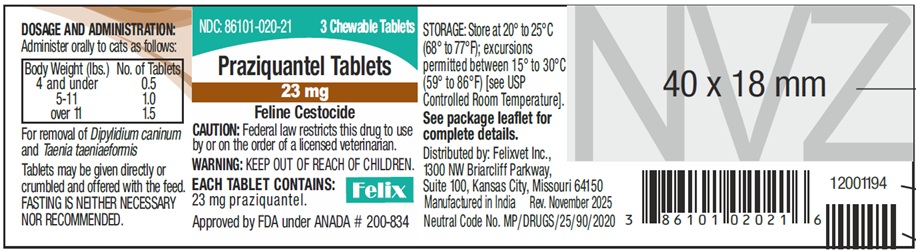 DRUG LABEL: Praziquantel
NDC: 86101-020 | Form: TABLET, CHEWABLE
Manufacturer: FELIX PHARMACEUTICALS PRIVATE LIMITED
Category: animal | Type: Prescription Animal Drug Label
Date: 20260113

ACTIVE INGREDIENTS: PRAZIQUANTEL 23 mg/1 1

Praziquantel Tablets
23 mg
Feline Cestocide

SPL UNCLASSIFIED SECTION

CAUTION: Federal law restricts this drug to use by or on the order of a licensed veterinarian.
Each Chewable Tablet contains 23 mg praziquantel.

DESCRIPTION

Praziquantel Tablets 23 mg Feline Cestocide are sized for easy oral administration to either adult cats or kittens. The tablets may be crumbled and mixed with the feed.

INDICATIONS

Praziquantel Tablets 23 mg Feline Cestocide are indicated for the removal of the following canine cestodes: Dipylidium caninum and Taenia,taeniaeformis.

CONTRAINDICATIONS

There are no known contraindications to the use of praziquantel in cats.

ACTION

Praziquantel Tablets are absorbed, metabolized in the liver and excreted in the bile. Upon entering the digestive tract from the bile, cestocidal activity is exhibited.^1
Following exposure to praziquantel, the tapeworm loses its ability to resist digestion by the mammalian host. Because of this, whole tapeworms, including the scolex, are very rarely passed after administration of praziquantel. In many instances only disintegrated and partially digested pieces of tapeworms will be seen in the stool. The majority of tapeworms killed are digested and are not found in the feces.

USE DIRECTIONS

Praziquantel Tablets 23 mg Feline Cestocide may be administered directly per os or crumbled and mixed with the feed. The recommended dosage of praziquantel varies according to body weight. Smaller animals require a relatively larger dosage because of their higher metabolic rate. The optimum dose for each individual animal will be achieved by utilizing the following dosage schedule:

Cats and Kittens*
4 pound and under | ½ tablet
5-11 pounds. | 1 tablet
Over 11 pounds | 1½ tablets

*Not intended for use in kittens less than 6 weeks of age.

FASTING

The recommended dosage of praziquantel is not affected by the presence or absence of food in the gastrointestinal tract, therefore, FASTING IS NEITHER NECESSARY NOR RECOMMENDED.

RETREATMENT

For those animals maintained on premises where reinfections are likely to occur, clients should be instructed in the steps necessary to prevent reinfection; otherwise, retreatment may be necessary. This is especially true in cases of Dipylidium caninum infections where reinfection is almost certain to occur if ﬂeas are not removed from the animal and its environment.

ANIMAL SAFETY

The safety index has been derived from controlled safety evaluations, clinical trials and prior approved use in foreign countries.

Dosages of 5 times the labeled rate at 14 day intervals to cats as young as 5½ weeks did not produce clinical signs of toxicity. No significant clinical chemistry, hematological, or histopathological changes occurred. Symptoms of gross overdosage include vomition, salivation, diarrhea and depression.

PREGNANCY

Praziquantel tablets have been tested in breeding and pregnant dogs. No adverse effects were noted.

ADVERSE REACTIONS

One instance of diarrhea and one of salivation (1.5%) were reported during the ﬁeld trials in which 135 cats were administered praziquantel tablets 23 feline cestocide.

CONTACT INFORMATION

Contact Felix Pharmaceuticals Private Limited at 1-833-571-1525. To report suspected adverse drug experiences, contact Felix Pharmaceuticals Private
Limited at 1-833-571-1525. For additional information about reporting adverse drug experiences for animal drugs, contact FDA at 1-888-FDA-VETS or http://www.fda.gov/reportanimalae
To obtain a Safety Data Sheet(s), contact Felix Pharmaceuticals Private Limited at 1-833-571-1525.

WARNING

Keep out of the reach of children. Not for human use.

STORAGE

Store at 20° to 25°C (68° to 77°F); excursions permitted between 15° to 30°C (59° to 86°F) [see USP Controlled Room Temperature].

HOW SUPPLIED

Bottle of 3, 50 and 150 scored tablets.

Each scored tablet contains 23 mg praziquantel.

NDC Number | Tablet Size | Tablets/Bottle
86101-020-21 | 23 mg | 3 Tablets
86101-020-50 | 23 mg | 50 Tablets
86101-020-13 | 23 mg | 150 Tablets

REFERENCES

^1Andrews, P. Pharmacokinetic Studies with Droncit® in Animals Using a Biological Assay. Veterinary Medical Review 2/76: 154-165.

Approved by FDA under ANADA # 200-834

Distributed by:
Felixvet Inc.,
1300 NW Briarcliff Parkway,
Suite 100, Kansas City, Missouri 64150

Made in India

Neutral Code No. MP/DRUGS/25/90/2020

Rev. November 2025

PACKAGE LABEL.PRINCIPAL DISPLAY PANEL

NDC 86101-020-21

Praziquantel Tablets

23 mg

Feline Cestocide

CAUTION: Federal (U.S.A) law restricts this drug to use by or on the order of a licensed veterinarian.

WARNING: KEEP OUT OF REACH OF CHILDREN. NOT FOR HUMAN USE.

EACH TABLET CONTAINS: 23 mg praziquantel

3 Chewable Tablets

Approved by FDA under ANADA # 200-834

PACKAGE LABEL.PRINCIPAL DISPLAY PANEL

NDC 86101-020-50

Praziquantel Tablets

23 mg

Feline Cestocide

CAUTION: Federal (U.S.A) law restricts this drug to use by or on the order of a licensed veterinarian.

WARNING: KEEP OUT OF REACH OF CHILDREN. NOT FOR HUMAN USE.

EACH TABLET CONTAINS: 23 mg praziquantel

50 Chewable Tablets

Approved by FDA under ANADA # 200-834

PACKAGE LABEL.PRINCIPAL DISPLAY PANEL

NDC 86101-020-13

Praziquantel Tablets

23 mg

Feline Cestocide

CAUTION: Federal (U.S.A) law restricts this drug to use by or on the order of a licensed veterinarian.

WARNING: KEEP OUT OF REACH OF CHILDREN. NOT FOR HUMAN USE.

EACH TABLET CONTAINS: 23 mg praziquantel

150 Chewable Tablets

Approved by FDA under ANADA # 200-834